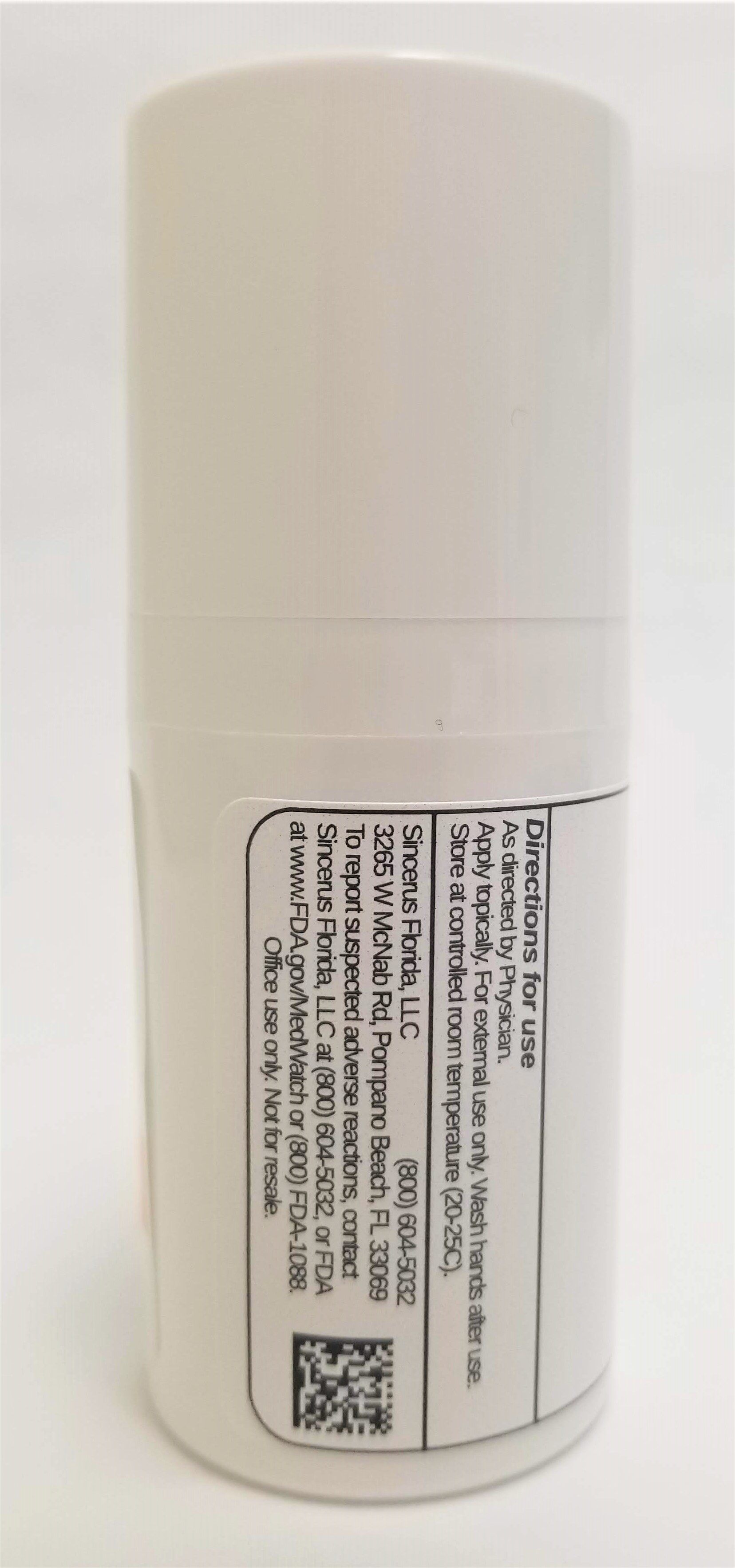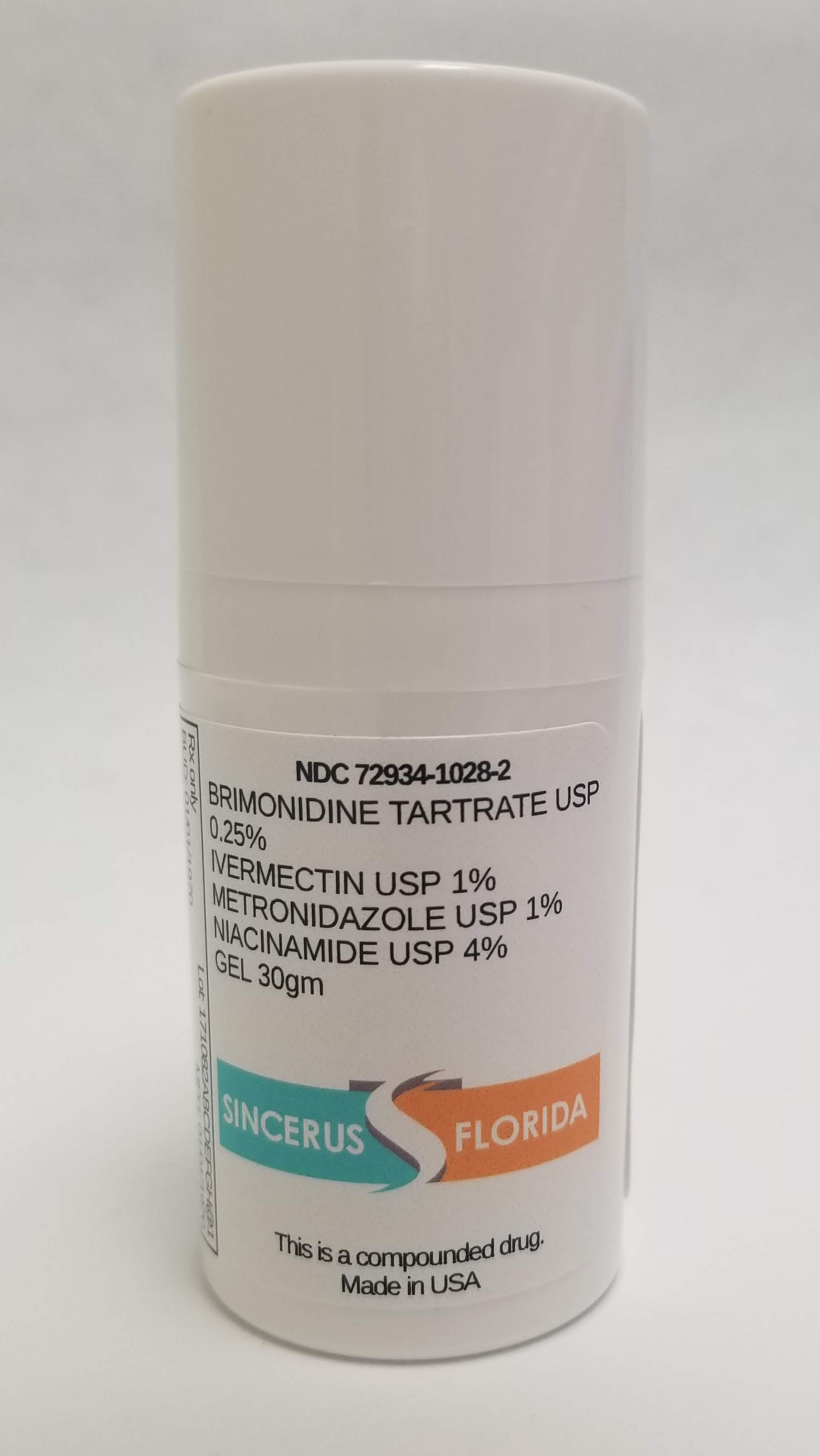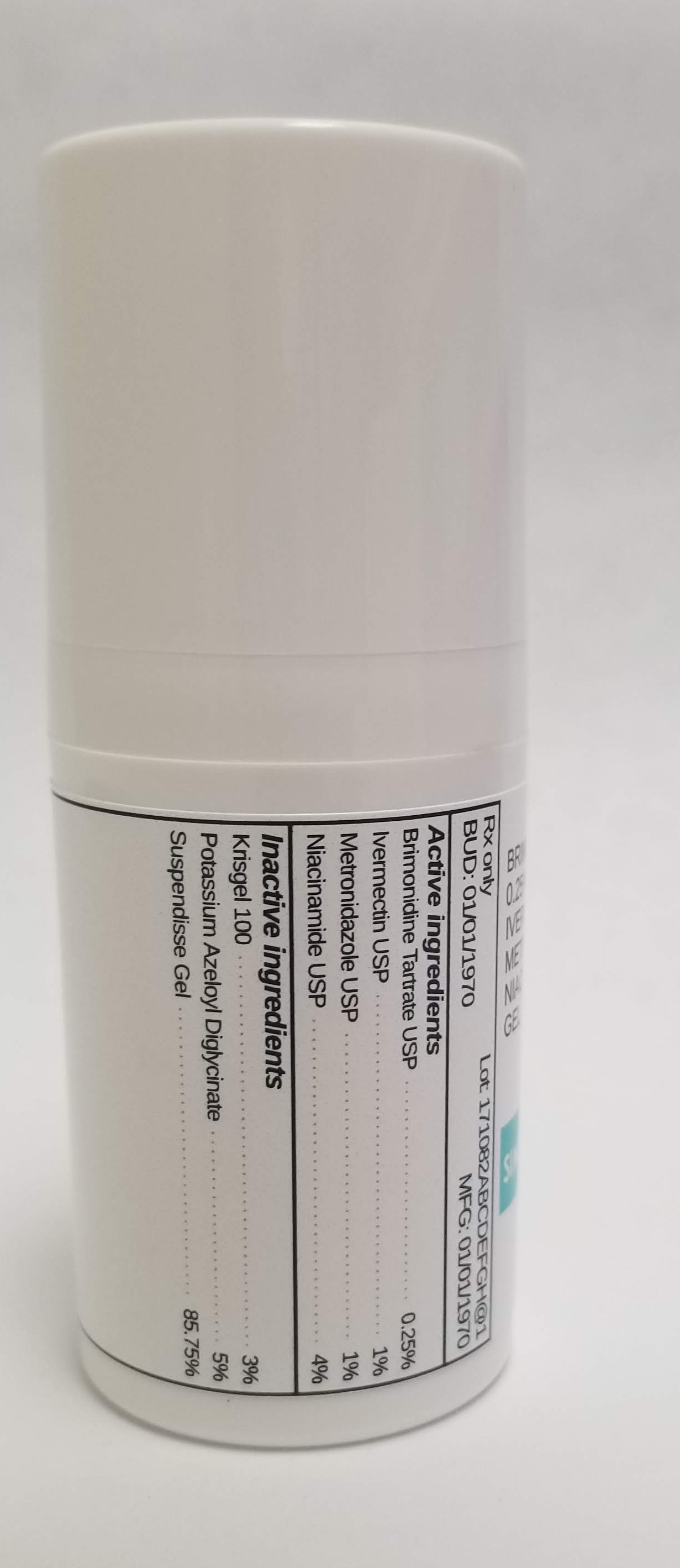 DRUG LABEL: BRIMONIDINE TARTRATE 0.25% / IVERMECTIN 1% / METRONIDAZOLE 1% / NIACINAMIDE 4%
NDC: 72934-1028 | Form: GEL
Manufacturer: Sincerus Florida, LLC
Category: prescription | Type: HUMAN PRESCRIPTION DRUG LABEL
Date: 20190515

ACTIVE INGREDIENTS: BRIMONIDINE TARTRATE 0.25 g/100 g; METRONIDAZOLE 1 g/100 g; NIACINAMIDE 4 g/100 g; IVERMECTIN 1 g/100 g

BRIMONIDINE TARTRATE 0.25% / IVERMECTIN 1% / METRONIDAZOLE 1% / NIACINAMIDE 4%